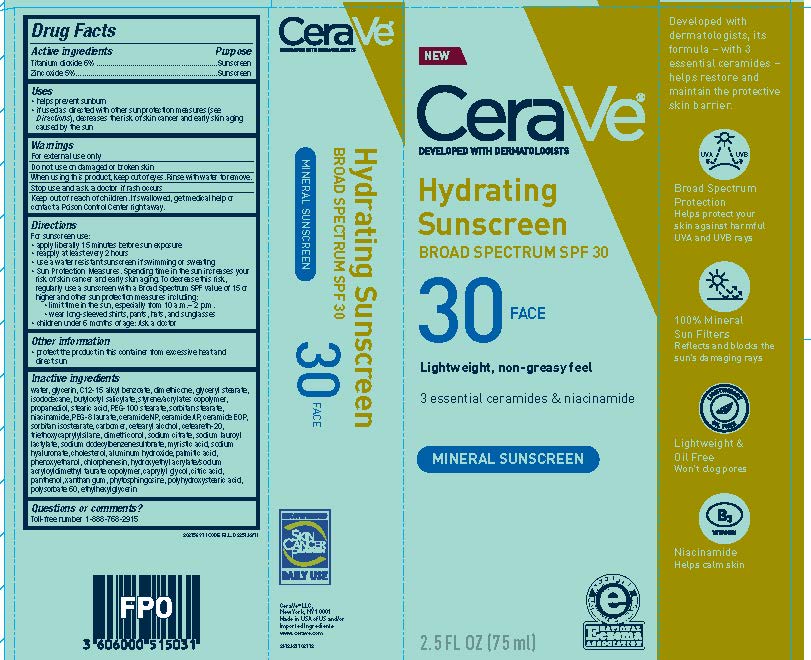 DRUG LABEL: CERAVE DEVELOPED WITH DERMATOLOGISTS HYDRATING SUNSCREEN SPF 30 FACE LIGHTWEIGHT, NON-GREASY FEEL 3 ESSENTIAL CERAMIDES NIACINAMIDE MINERAL SUNSCREEN
NDC: 49967-150 | Form: LOTION
Manufacturer: L'Oreal USA Products Inc
Category: otc | Type: HUMAN OTC DRUG LABEL
Date: 20231231

ACTIVE INGREDIENTS: TITANIUM DIOXIDE 60 mg/1 mL; ZINC OXIDE 50 mg/1 mL
INACTIVE INGREDIENTS: WATER; GLYCERIN; ALKYL (C12-15) BENZOATE; DIMETHICONE; ISODODECANE; GLYCERYL MONOSTEARATE; BUTYLOCTYL SALICYLATE; PROPANEDIOL; STEARIC ACID; PEG-100 STEARATE; SORBITAN MONOSTEARATE; NIACINAMIDE; PEG-8 LAURATE; CERAMIDE NP; CERAMIDE AP; CERAMIDE 1; SORBITAN ISOSTEARATE; CARBOXYPOLYMETHYLENE; CETOSTEARYL ALCOHOL; POLYOXYL 20 CETOSTEARYL ETHER; TRIETHOXYCAPRYLYLSILANE; SODIUM CITRATE; SODIUM LAUROYL LACTYLATE; SODIUM DODECYLBENZENESULFONATE; MYRISTIC ACID; HYALURONATE SODIUM; CHOLESTEROL; ALUMINUM HYDROXIDE; PALMITIC ACID; PHENOXYETHANOL; CHLORPHENESIN; HYDROXYETHYL ACRYLATE/SODIUM ACRYLOYLDIMETHYL TAURATE COPOLYMER (45000 MPA.S AT 1%); CAPRYLYL GLYCOL; CITRIC ACID ACETATE; PANTHENOL; XANTHAN GUM; PHYTOSPHINGOSINE; POLYHYDROXYSTEARIC ACID STEARATE; POLYSORBATE 60; ETHYLHEXYLGLYCERIN

Drug Facts

Active ingredients

Titanium dioxide 6%

Zinc oxide 5%

Purpose

Sunscreen

Uses

- helps prevent sunburn
- if used as directed with other sun protection measures (see Directions), decreases the risk of skin cancer and early skin aging caused by the sun

Warnings

For external use only

Do not use

on damaged or broken skin

Stop use and ask a doctor if

rash occurs

Keep out of reach of children.

If swallowed, get medical help or contact a Poison Control Center right away.

Directions

For sunscreen use:

- apply liberally 15 minutes before sun exposure
- reapply at least every 2 hours
- use a water resistant sunscreen if swimming or sweating
- Sun Protection Measures. Spending time in the sun increases your risk of skin cancer and early skin aging. To decrease this risk, regularly use a sunscreen with a Broad Spectrum SPF value of 15 or higher and other sun protection measures including:
- limit time in the sun, especially from 10 a.m.-2p.m.
- wear long-sleeved shirts, pants, hats and sunglasses
- children under 6 months of age: Ask a doctor

Other information

- protect the product in this container from excessive heat and direct sun

Inactive ingredients

water, glycerin, C12-15 alkyl benzoate, dimethicone, glyceryl stearate, isododecane, butyloctyl salicylate, styrene/acrylates copolymer, propanediol, stearic acid, PEG-100 sterate, sorbitan stearate, niacinamide, acrylates/dimethicone copolymer, PEG-8 laurate, ceramide NP, ceramide AP, ceramide EOP, sorbitan isostearate, carbomer, cetearyl alcohol, ceteareth-20, triethoxycaprylylsilane, dimethiconol, sodium citrate, sodium lauroyl lactylate, sodium dodecylbenzenesulfonate, myristic acid, sodium hyaluronate, cholesterol, aluminum hydroxide, palmitic acid, phenoxyethanol, chlorphenesin, hydroxyethyl acrylate/sodium acryloyldimethyl taurate copolymer, caprylyl glycol, citric acid, panthenol, xanthan gum, phytosphingosine, polyhydroxystearic acid, polysorbate 60, ethylhexylglycerin